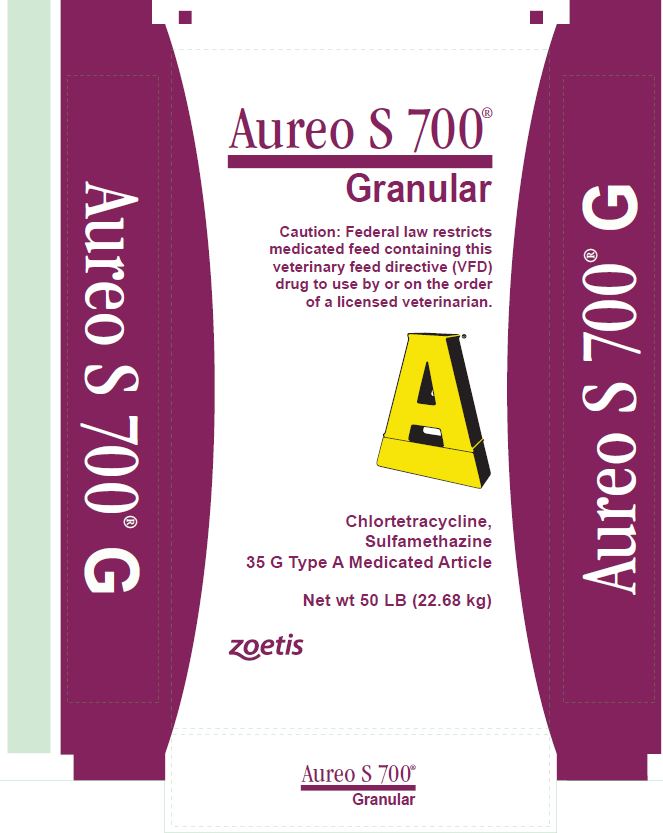 DRUG LABEL: AureoS 700
NDC: 54771-1007 | Form: GRANULE
Manufacturer: Zoetis Inc.
Category: animal | Type: VFD TYPE A MEDICATED ARTICLE ANIMAL DRUG LABEL
Date: 20170512

ACTIVE INGREDIENTS: CHLORTETRACYCLINE HYDROCHLORIDE 35 g/0.45 kg; SULFAMETHAZINE 35 g/0.45 kg
INACTIVE INGREDIENTS: CALCIUM SULFATE

Aureo S 700®
Granular

Chlortetracycline, sulfamethazine
35 G Type A Medicated Article

Caution: Federal law restricts medicated feed containing this veterinary feed directive (VFD) drug to use by or on the order of a licensed veterinarian.

Active drug ingredients

Chlortetracycline calcium complex
equivalent to chlortetracycline HCl ................................................................. 35 g/lb

Sulfamethazine .................................................................................... 7.7% (35 g/lb)

Ingredients

Calcium sulfate and dried Streptomyces aureofaciens fermentation product.

PURPOSE

For use in the manufacture of medicated beef cattle feeds

Indications

As an aid in the maintenance of weight gains in the presence of respiratory disease such as shipping fever.

Mixing directions

Mix sufficient Aureo S 700 in the feed to supply 350 mg of Aureomycin chlortetracycline and 350 mg of sulfamethazine per head per day. The following table shows the amounts of Aureo S 700 needed for the various quantities of supplement.

Aureo S 700 (lb/ton of Supplement) | Supplement Will Contain (g/ton) |  | Feed Supplement at (lb/head/day)
Aureo S 700 (lb/ton of Supplement) | Chlortetracycline | Sulfamethazine | Feed Supplement at (lb/head/day)
40 | 1400 | 1400 | 0.5
20 | 700 | 700 | 1
10 | 350 | 350 | 2
5 | 175 | 175 | 4
4 | 140 | 140 | 5
2 | 70 | 70 | 10
1 | 35 | 35 | 20

Feeding instructions

Feed for 28 days.

Warning

Withdraw 7 days prior to slaughter.

A withdrawal period has not been established for this product in pre-ruminating calves.

Do not use in calves to be processed for veal.

Restricted Drug (California) - use only as directed. Not for human use.

Store below 25°C (77°F), excursions permitted to 37°C (99°F).

NADA #35-805, Approved by FDA

Distributed by: Zoetis Inc.

Kalamazoo, MI 49007

Net wt 50 LB (22.68 kg)

Made in USA

PRINCIPAL DISPLAY PANEL - 50 LB Bag

Aureo S 700®
Granular

Zoetis

Chlortetracycline,
sulfamethazine
35 G Type A Medicated Article

Net wt 50 LB (22.68 kg)

Zoetis

Aureo S 700®
Granular